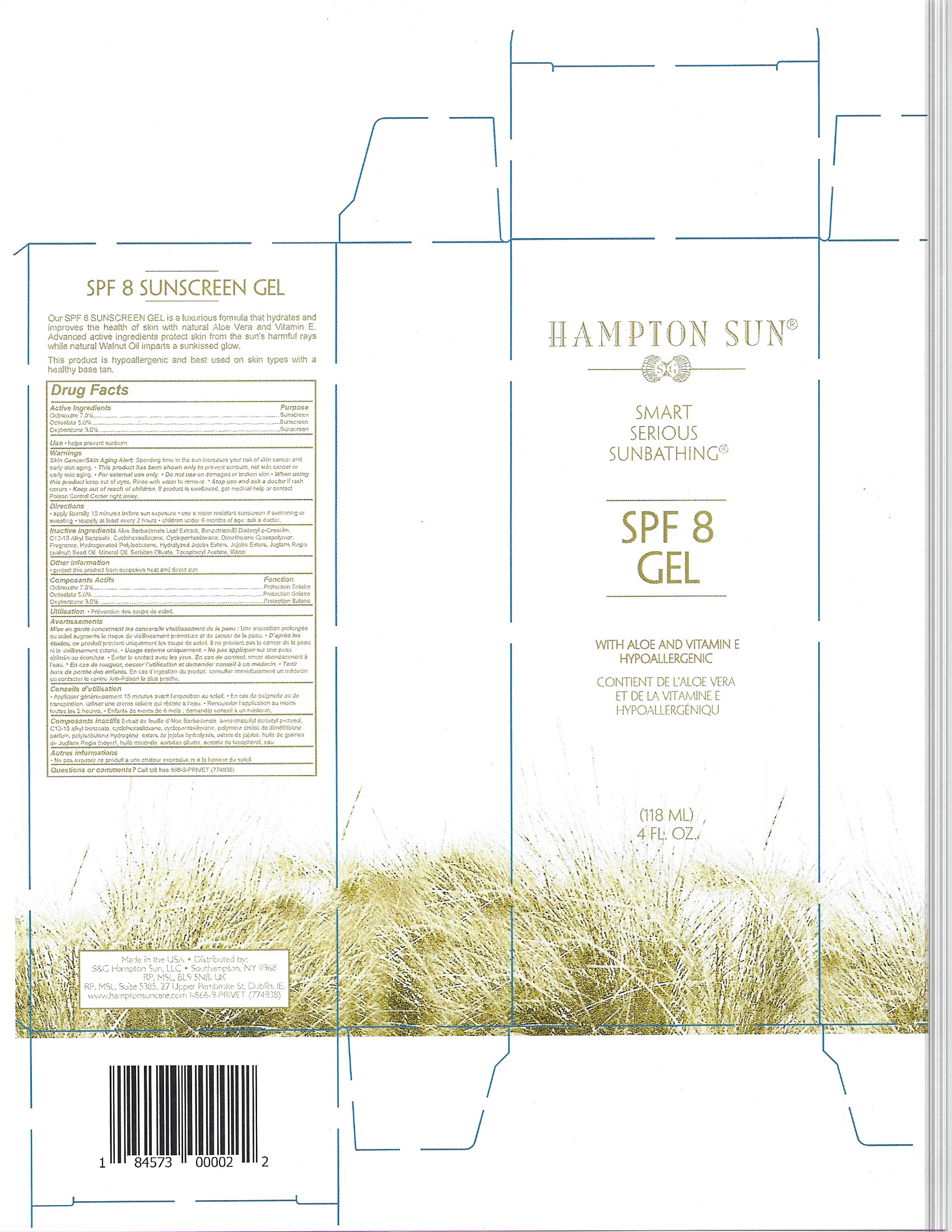 DRUG LABEL: HAMPTON SUN
NDC: 87170-002 | Form: SPRAY
Manufacturer: Hampton Sun
Category: otc | Type: HUMAN OTC DRUG LABEL
Date: 20251027

ACTIVE INGREDIENTS: OCTISALATE 5 g/100 g; OXYBENZONE 3 g/100 g; OCTINOXATE 7 g/100 g
INACTIVE INGREDIENTS: ALOE; C12-15 ALCOHOLS; TRIEPOXYCYCLOHEXASILANE; DIMETHICONE CROSSPOLYMER (450000 MPA.S AT 12% IN CYCLOPENTASILOXANE); DIMETHICONE/VINYL DIMETHICONE CROSSPOLYMER (SOFT PARTICLE); HYDROLYZED JOJOBA ESTERS (POTASSIUM SALTS); WALNUT OIL; SORBITAN OLIVATE; BENZOTRIAZOLYL DODECYL P-CRESOL; MINERAL OIL; WATER

HAMPTON SUN SPF 8 SUNSCREEN GEL

Active Ingredients:

Octinoxate - 7.50%

Octisalate - 5.00%

Oxybenzone - 3.00%

PURPOSE

Octinoxate - 7.50% .....................Sunscreen.

Octisalate - 5.00% ......................Sunscreen.

Oxybenzone - 3.00% ..................Sunscre.en.

INDICATIONS AND USAGE

Use • helps prevent sunburn.

Warnings

Skin cancer/Skin Aging alert

For external use only

Do noy use on Damage or broken skin

keep out of eyes. Rinse with water to remove.

Stop use and ask a doctor if rash occurs.

Keep out of reach of children. If swallowed, get medical help or contact a Poison Control Center immediately.

DIRECTIONS

• Apply liberally 15 minutes before sun exposure.

•Use a water resistant sunscreen if swimming or sweating.

•Reapply at least every 2 hours

•Children under 6 months of age: ask a doctor.

Inactive Ingredients:

Aloe Barbadensis Leaf Extract, Benzotriazolyl Dodecyl p-Cresol, C12-15 Alkyl Benzoate, Cyclohexasiloxanel, Cyclopentasiloxane

Dimethicone Crosspolymer, Fragrance, Hydrogenated Polyisobutene, Hydrolyzed Jojoba Esters, Jojoba Esters, Juglans Regia (Walnut) Seed Oil, Mineral OilSorbitan Olivate, Tocopheryl Acetatel, Water